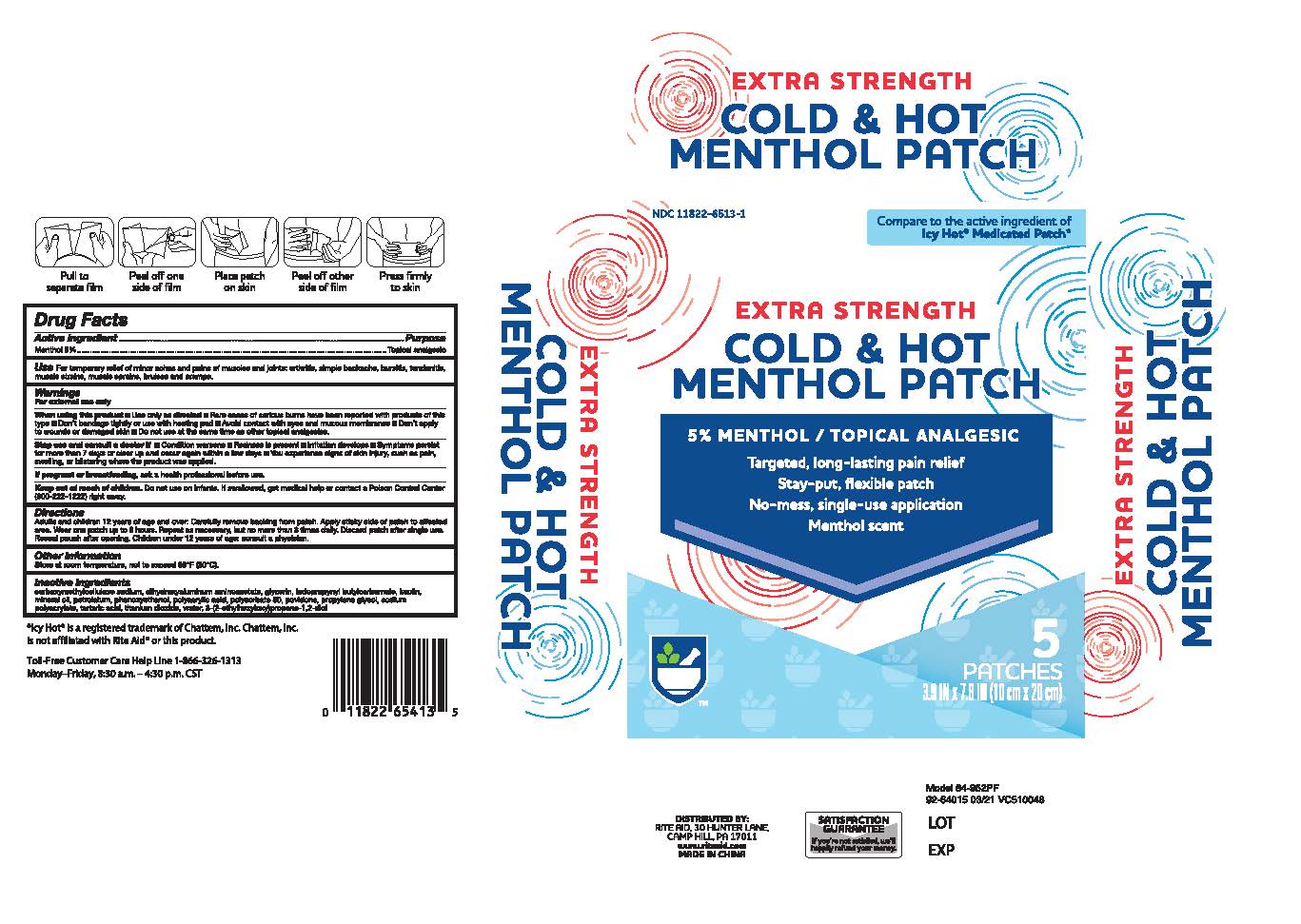 DRUG LABEL: Extra Strength Cold and Hot Menthol Patch
NDC: 11822-6513 | Form: PATCH
Manufacturer: Rite Aid Corporation
Category: otc | Type: HUMAN OTC DRUG LABEL
Date: 20241218

ACTIVE INGREDIENTS: MENTHOL, UNSPECIFIED FORM 5 g/100 g
INACTIVE INGREDIENTS: CARBOXYMETHYLCELLULOSE SODIUM; PETROLATUM; DIHYDROXYALUMINUM AMINOACETATE; GLYCERIN; KAOLIN; POLYACRYLIC ACID (8000 MW); PHENOXYETHANOL; POLYSORBATE 80; POLYETHYLENE GLYCOL 400; POVIDONE, UNSPECIFIED; SODIUM POLYACRYLATE (8000 MW); TARTARIC ACID; TITANIUM DIOXIDE; WATER; IODOPROPYNYL BUTYLCARBAMATE; ETHYLHEXYLGLYCERIN; MINERAL OIL

Extra Strength Cold & Hot Menthol Patch

Active Ingredients

Menthol 5% . . . . . . . . . . . . . . . . . . . . . . . . . . . . . . Topical Analgesic

Uses

Temporarily relieves minor pain.

Warnings

For external use only.

When using this product

■ use only as directed

■ rear cases of serious burns have been reported with products of this type

■ Don't bandage tightly or use with a heating pad

■ Avoid contact with the eyes and mucous membranes

■Don't apply to wounds or damaged skin

■ Do not use at the same time as other topical analgesics

Stop use and consult a doctor

■ condition worsens

■ redness is present

■ irritation develops

■ symptoms persist for more than 7 days or clear up and occur again within a few days

■ you experience signs of skin injury, such as pain, swelling or blistering where the product was applied.

PREGNANCY OR BREAST FEEDING

If pregnant or breastfeeding, ask a health professional before use.

Keep out of reach of children and pets.

If swallowed, get medical help or contact a Poison Control Center 800-222-1222 right away.

Dosage and Administration

Directions Adults and children 12 years of age and over :

■ Carefully remove backing from patch

■ Apply sticky side of patch to affected area.

■ Wear 1 patch up to 8 hours. Repeat as necessary, but no more than 3 times daily..

■ Discard patch after single use.

■Reseal pouch after opening.

■Children under 12 years of age: consult a physician.

Other Safety Information

Store at room temperature, not to exceed 86F (30C)

Inactive Ingredients

Carboxymethylcellulose Sodium, Dihydroxyaluminum Aminoacetate, Glycerin, iodopropynyl butylcarbamate, Kaolin, mineral oil, petrolatum, Phenoxyethanol, polyacrylic acid, Polysorbate 80, Povidone, Propylene Glycol, Sodium Polyacrylate, Tartaric Acid, Titanium Dioxide, Water, 3-(2-ethylhexyloxy)propane-1,2-diol

Uses

Temporarily relieves minor pain.